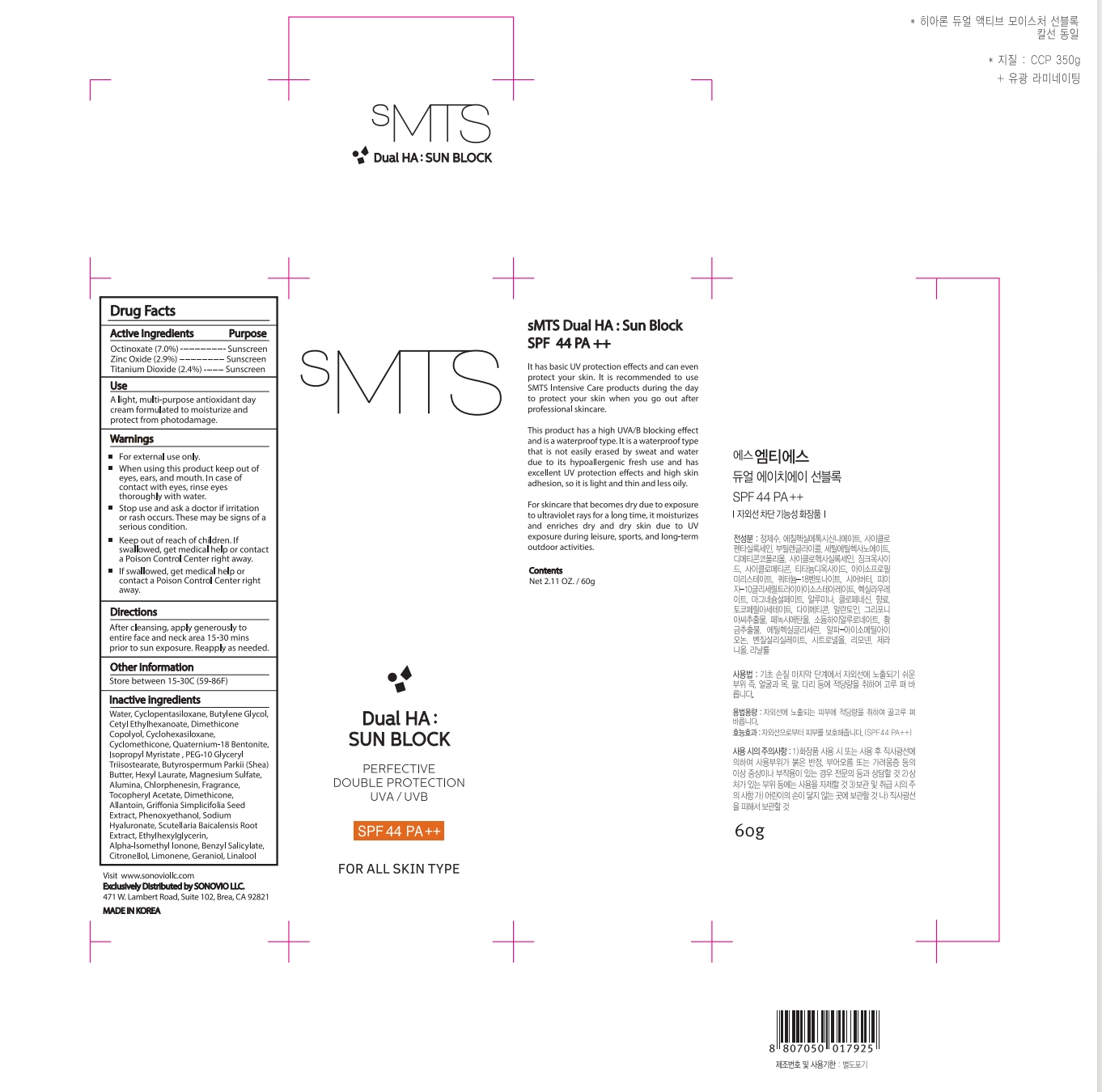 DRUG LABEL: sMTS Dual HA SUN BLOCK
NDC: 84609-001 | Form: CREAM
Manufacturer: Sonovio LLC
Category: otc | Type: HUMAN OTC DRUG LABEL
Date: 20240808

ACTIVE INGREDIENTS: ZINC OXIDE 2.94 g/100 g; TITANIUM DIOXIDE 2.4 g/100 g; OCTINOXATE 7 g/100 g
INACTIVE INGREDIENTS: ISOMETHYL-.ALPHA.-IONONE; PHENOXYETHANOL; LIMONENE, (+)-; BUTYROSPERMUM PARKII (SHEA) BUTTER UNSAPONIFIABLES; CHLORPHENESIN; .BETA.-CITRONELLOL, (R)-; BUTYLENE GLYCOL; CETYL ETHYLHEXANOATE; CYCLOMETHICONE 6; BENTOQUATAM; ISOPROPYL MYRISTATE; PEG-10 GLYCERYL TRIISOSTEARATE; HYALURONATE SODIUM; SCUTELLARIA BAICALENSIS ROOT; LINALOOL, (+/-)-; GRIFFONIA SIMPLICIFOLIA SEED; WATER; CYCLOMETHICONE 5; PEG/PPG-18/18 DIMETHICONE; ETHYLHEXYLGLYCERIN; MAGNESIUM SULFATE, UNSPECIFIED; ALPHA-TOCOPHEROL ACETATE; DIMETHICONE; ALLANTOIN; CYCLOMETHICONE; ALUMINUM OXIDE; BENZYL SALICYLATE; GERANIOL; HEXYL LAURATE

ACTIVE INGREDIENT

Octinoxate 7.0%

Zinc Oxide 2.94%

Titanium Dioxide 2.4%

PURPOSE

Sunscreen

Uses

A light, multi-purpose antioxidant day cream formulated to moisturize and protect from photodamage.

Warnings

①For external use only.
② When using this product keep out of eyes, ears, and mouth. In case of contact with eyes, rinse eyes thoroughly with water.
③Stop use and ask a doctor if irrrtion or rash occurs. These may be signs of a serious condition.
④Keep out of reach of children. If swallowed, get medical help or contact a Poison Control Center right away,
⑤If swallowed, get medical help or contact a Poison Control Center rightaway.

Do not use on damaged or broken skin.

Keep out of reach of children. If swallowed, get medical help or contact a Poison Control Center right away,

Directions

After cleansing, apply generously to entire face and neck area 15-30 mins prior to sun exposure. Reapply as needed.

Other information

Store between 15-30C (59-86F)

Inactive Ingredients

Water, Cyclopentasiloxane, Butylene Glycol, Cetyl Ethylhexanoate, Dimethicone Copolyol, Cyclohexasiloxane,

Cyclomethicone, Quaternium-18 Bentonite, lsopropyl Myristate , PEG-10 Glyceryl Triisostearate,

Butyrospermum Parkii (Shea) Butter, Hexyl Laurate, Magnesium Sulfate, Alumina, Chlorphenesin, Fragrance,

Tocopheryl Acetate, Dimethicone, Allantoin, Griffonia Simplicifolia Seed Extract, Phenoxyethanol, Sodium
Hyaluronate, Scutellaria Baicalensis Root Extract, Ethylhexylglycerin, Alpha-lsomethyl lonone, Benzyl Salicylate,

Citronellol, Limonene, Geraniol, Linalool